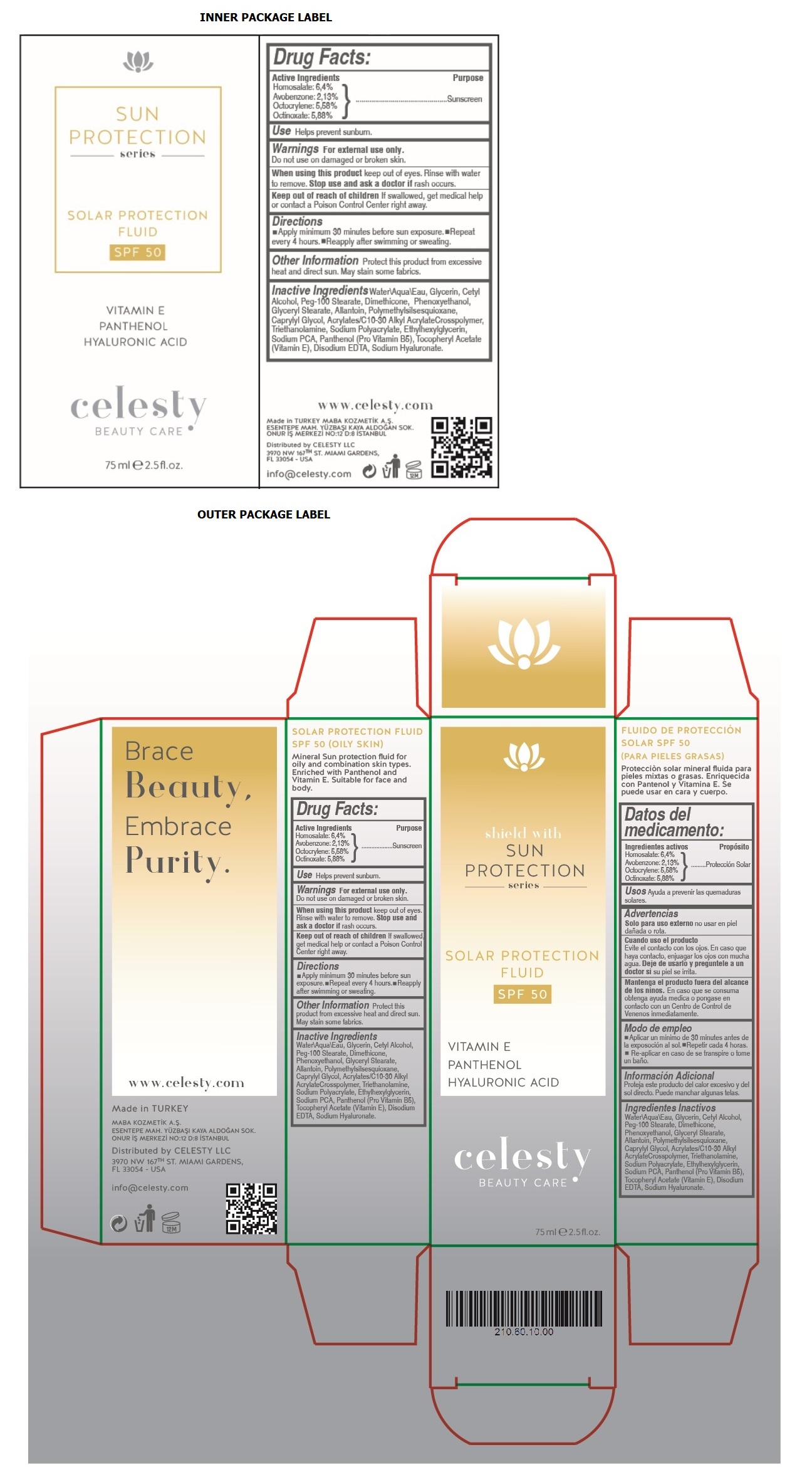 DRUG LABEL: Celesty
NDC: 81120-109 | Form: CREAM
Manufacturer: MABA KOZMETIK LIMITED SIRKETI
Category: otc | Type: HUMAN OTC DRUG LABEL
Date: 20201208

ACTIVE INGREDIENTS: HOMOSALATE 64 mg/1 mL; AVOBENZONE 21.3 mg/1 mL; OCTOCRYLENE 55.8 mg/1 mL; OCTINOXATE 58.8 mg/1 mL
INACTIVE INGREDIENTS: WATER; GLYCERIN; CETYL ALCOHOL; PEG-100 STEARATE; DIMETHICONE; PHENOXYETHANOL; GLYCERYL MONOSTEARATE; ALLANTOIN; POLYMETHYLSILSESQUIOXANE (4.5 MICRONS); CAPRYLYL GLYCOL; CARBOMER INTERPOLYMER TYPE A (ALLYL SUCROSE CROSSLINKED); TROLAMINE; SODIUM POLYACRYLATE (2500000 MW); ETHYLHEXYLGLYCERIN; SODIUM PYRROLIDONE CARBOXYLATE; PANTHENOL; .ALPHA.-TOCOPHEROL ACETATE; EDETATE DISODIUM ANHYDROUS; HYALURONATE SODIUM

Celesty SUN PROTECTION series SOLAR PROTECTION FLUID SPF 50

Active Ingredients

Homosalate: 6,4%

Avobenzone: 2,13%

Octocrylene: 5,58%

Octinoxate: 5,88%

Purpose

Sunscreen

Use

Helps prevent sunburn.

Warnings

For external use only.

Do not use on damaged or broken skin.

When using this product keep out eyes. Rinse with water to remove. Stop use and ask a doctor if rash occurs.

Keep out of reach of children If swallowed, get medical help or contact a Poison Control Center right away.

Directions

• Apply minimum 30 minutes before sun exposure. • Repeat every 4 hours. • Reapply after swimming or sweating.

Other Information

Protect this product from excessive heat and direct sun. May stain some fabrics.

Inactive Ingredients

Water\Aqua\Eau, Glycerin, Cetyl Alcohol, Peg-100 Stearate, Dimethicone, Phenoxyethanol, Glyceryl Stearate, Allantoin, Polymethylsilsesquioxane, Caprylyl Glycol, Acrylates/C 10-30 Alkyl Acrylate Crosspolymer, Triethanolamine, Sodium Polyacrylate, Ethylhexylglycerin, Sodium PCA, Panthenol (Pro Vitamin B5), Tocopheryl Acetate (Vitamin E), Disodium EDTA, Sodium Hyaluronate.

shield with SUN PROTECTION series

VITAMIN E

PANTHENOL

HYALURONIC ACID

BEAUTY CARE

SOLAR PROTECTION FLUID SPF 50 (OILY SKIN)

Mineral Sun protection fluid for oily and combination skin types. Enriched with Panthenol and Vitamin E. Suitable for face and body.

Brace Beauty, Embrace Purity.

www.celesty.com

Made in TURKEY

MABA KOZMETIK A.S.

ESENTEPE MAH. YUZBASI KAYA ALDOGAN SOK.

ONUR IS MERKEZI NO:12 D:8 ISTANBUL

Distributed by CELESTY LLC

3970 NW 167TH ST. MIAMI GARDENS,

FL 33054 - USA

info@celesty.com